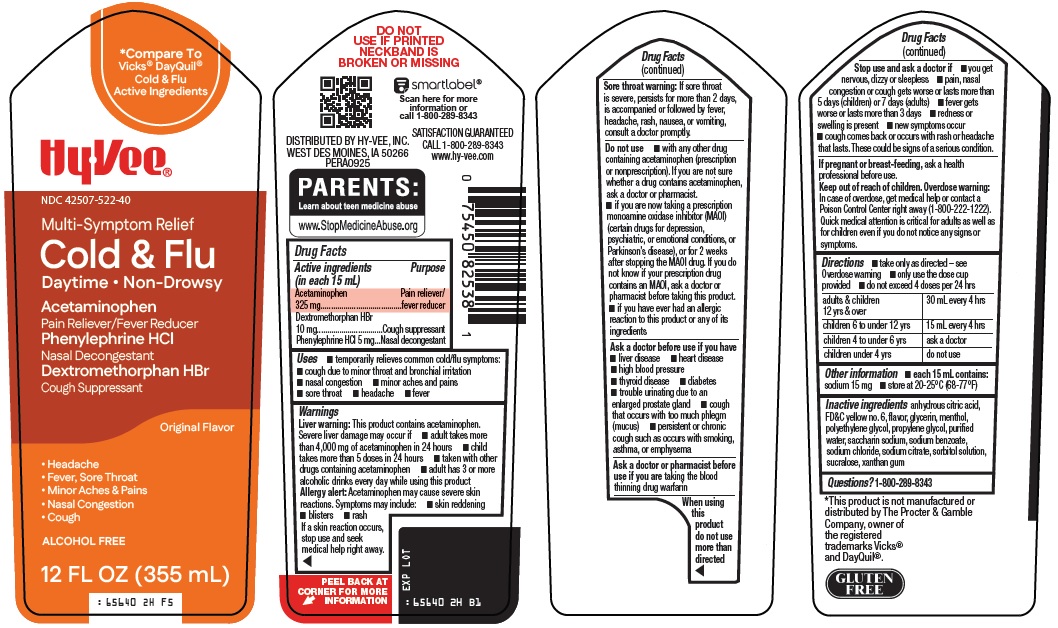 DRUG LABEL: Cold and Flu
NDC: 42507-522 | Form: SOLUTION
Manufacturer: HyVee Inc
Category: otc | Type: HUMAN OTC DRUG LABEL
Date: 20260217

ACTIVE INGREDIENTS: ACETAMINOPHEN 325 mg/15 mL; DEXTROMETHORPHAN HYDROBROMIDE 10 mg/15 mL; PHENYLEPHRINE HYDROCHLORIDE 5 mg/15 mL
INACTIVE INGREDIENTS: ANHYDROUS CITRIC ACID; FD&C YELLOW NO. 6; GLYCERIN; MENTHOL, UNSPECIFIED FORM; POLYETHYLENE GLYCOL, UNSPECIFIED; PROPYLENE GLYCOL; WATER; SACCHARIN SODIUM; SODIUM BENZOATE; SODIUM CHLORIDE; SODIUM CITRATE, UNSPECIFIED FORM; SORBITOL SOLUTION; SUCRALOSE; XANTHAN GUM

Hy-Vee, Inc. Cold & Flu Drug Facts

Active ingredients (in each 15 mL)

Acetaminophen 325 mg

Dextromethorphan HBr 10 mg

Phenylephrine HCl 5 mg

Purpose

Pain reliever/fever reducer

Cough suppressant

Nasal decongestant

Uses

- temporarily relieves common cold/flu symptoms:
- cough due to minor throat and bronchial irritation
- nasal congestion
- minor aches and pains
- sore throat
- headache
- fever

Warnings

Liver warning: This product contains acetaminophen. Severe liver damage may occur if

- adult takes more than 4,000 mg of acetaminophen in 24 hours
- child takes more than 5 doses in 24 hours
- taken with other drugs containing acetaminophen
- adult has 3 or more alcoholic drinks every day while using this product

Allergy alert: Acetaminophen may cause severe skin reactions. Symptoms may include:

- skin reddening
- blisters
- rash

If a skin reaction occurs, stop use and seek medical help right away.

Sore throat warning: If sore throat is severe, persists for more than 2 days, is accompanied or followed by fever, headache, rash, nausea, or vomiting, consult a doctor promptly.

Do not use

- with any other drug containing acetaminophen (prescription or nonprescription). If you are not sure whether a drug contains acetaminophen, ask a doctor or pharmacist.
- if you are now taking a prescription monoamine oxidase inhibitor (MAOI) (certain drugs for depression, psychiatric, or emotional conditions, or Parkinson’s disease), or for 2 weeks after stopping the MAOI drug. If you do not know if your prescription drug contains an MAOI, ask a doctor or pharmacist before taking this product.
- if you have ever had an allergic reaction to this product or any of its ingredients

Ask a doctor before use if you have

- liver disease
- heart disease
- high blood pressure
- thyroid disease
- diabetes
- trouble urinating due to an enlarged prostate gland
- cough that occurs with too much phlegm (mucus)
- persistent or chronic cough such as occurs with smoking, asthma, or emphysema

Ask a doctor or pharmacist before use if you are

taking the blood thinning drug warfarin

When using this product

do not use more than directed

Stop use and ask a doctor if

- you get nervous, dizzy or sleepless
- pain, nasal congestion or cough gets worse or lasts more than 5 days (children) or 7 days (adults)
- fever gets worse or lasts more than 3 days
- redness or swelling is present
- new symptoms occur
- cough comes back or occurs with rash or headache that lasts. These could be signs of a serious condition.

If pregnant or breast-feeding,

ask a health professional before use.

Keep out of reach of children.

Overdose warning: In case of overdose, get medical help or contact a Poison Control Center right away (1-800-222-1222). Quick medical attention is critical for adults as well as for children even if you do not notice any signs or symptoms.

Directions

- take only as directed – see Overdose warning
- only use the dose cup provided
- do not exceed 4 doses per 24 hrs

adults & children 12 yrs & over | 30 mL every 4 hrs
children 6 to under 12 yrs | 15 mL every 4 hrs
children 4 to under 6 yrs | ask a doctor
children under 4 yrs | do not use

Other information

- each 15 mL contains: sodium 15 mg
- store at 20-25°C (68-77°F)

Inactive ingredients

anhydrous citric acid, FD&C yellow no. 6, flavor, glycerin, menthol, polyethylene glycol, propylene glycol, purified water, saccharin sodium, sodium benzoate, sodium chloride, sodium citrate, sorbitol solution, sucralose, xanthan gum

Questions?

1-800-289-8343

Principal Display Panel

Compare To Vicks® DayQuil® Cold & Flu Active Ingredients

Hy•Vee®

Multi-Symptom Relief

Cold & Flu

Daytime • Non-Drowsy

Acetaminophen

Pain Reliever/Fever Reducer

Phenylephrine HCl

Nasal Decongestant

Dextromethorphan HBr

Cough Suppressant

Original Flavor

• Headache

• Fever, Sore Throat

• Minor Aches & Pains

• Nasal Congestion

• Cough

ALCOHOL FREE

12 FL OZ (355 mL)